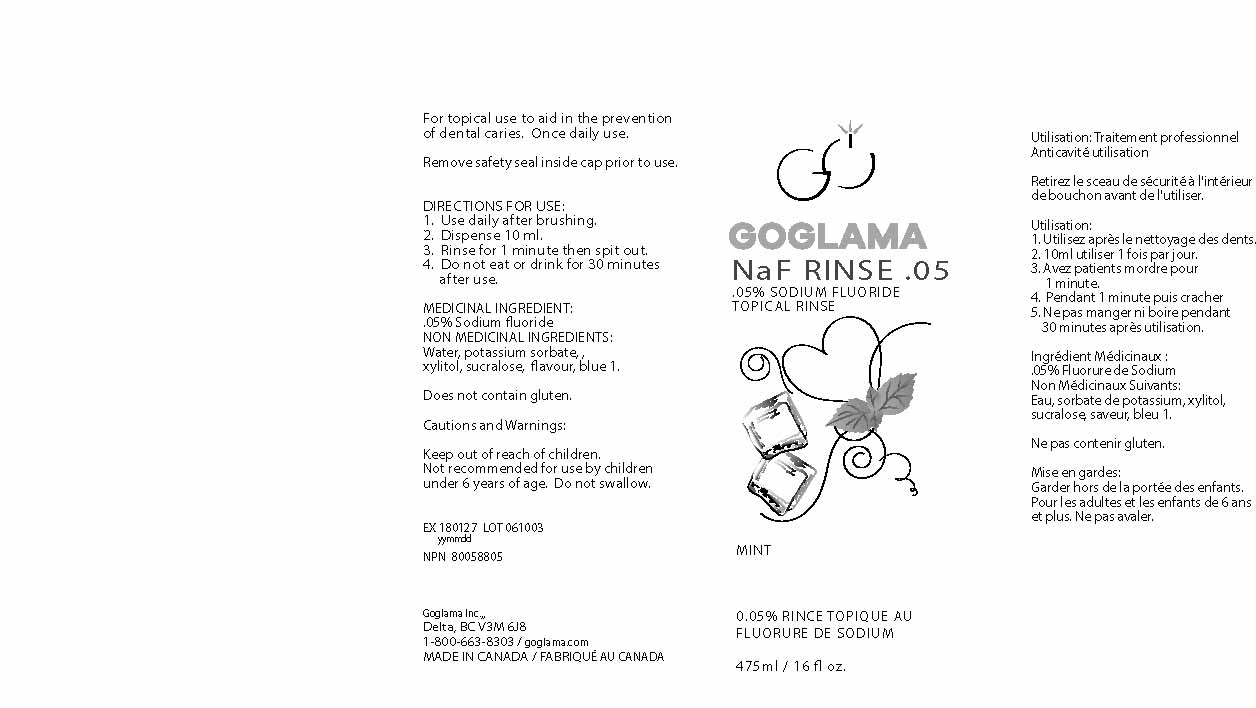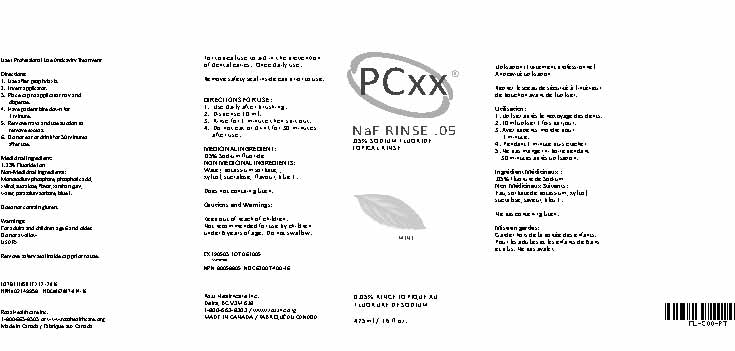 DRUG LABEL: GoGlama  NaF RNS Mint
NDC: 62007-700 | Form: RINSE
Manufacturer: Ross Healthcare Inc.
Category: otc | Type: HUMAN OTC DRUG LABEL
Date: 20171123

ACTIVE INGREDIENTS: SODIUM FLUORIDE 0.5 mg/1 mL
INACTIVE INGREDIENTS: POTASSIUM SORBATE 0.04 mg/1 mL; XYLITOL 0.5 mg/1 mL; SUCRALOSE 0.01 mg/1 mL

GoGlama NaF RNS Mint

DOSAGE AND ADMINISTRATION

Adults and children 6 years of age and older:

use once a day after brushing your teeth with a toothpaste
remove cap
hold bottle upright and squeeze. Fill to FILL LINE
pour out. Only the correct 10 milliliters dose will pour out
vigorously swish 10 milliliters of rinse between your teeth for 1 minute and then spit out
do not swallow the rinse
do not eat or drink for 30 minutes after rinsing
instruct children under 12 years of age in good rinsing habits (to minimize swallowing)
supervise children as necessary until capable of using without supervision

children under 6 years of age: consult a dentist or doctor.

Keep out of reach of children.

If more than used for rinsing is accidently swallowed, get medical help or contact Poison Control Center right away.

INACTIVE INGREDIENT

potassium sorbate, xylitol, sucralose, water

INDICATIONS AND USAGE

Aids in the prevention of dental cavities

ACTIVE INGREDIENT

Sodium Fluoride 0.05%

PURPOSE

Anticavity